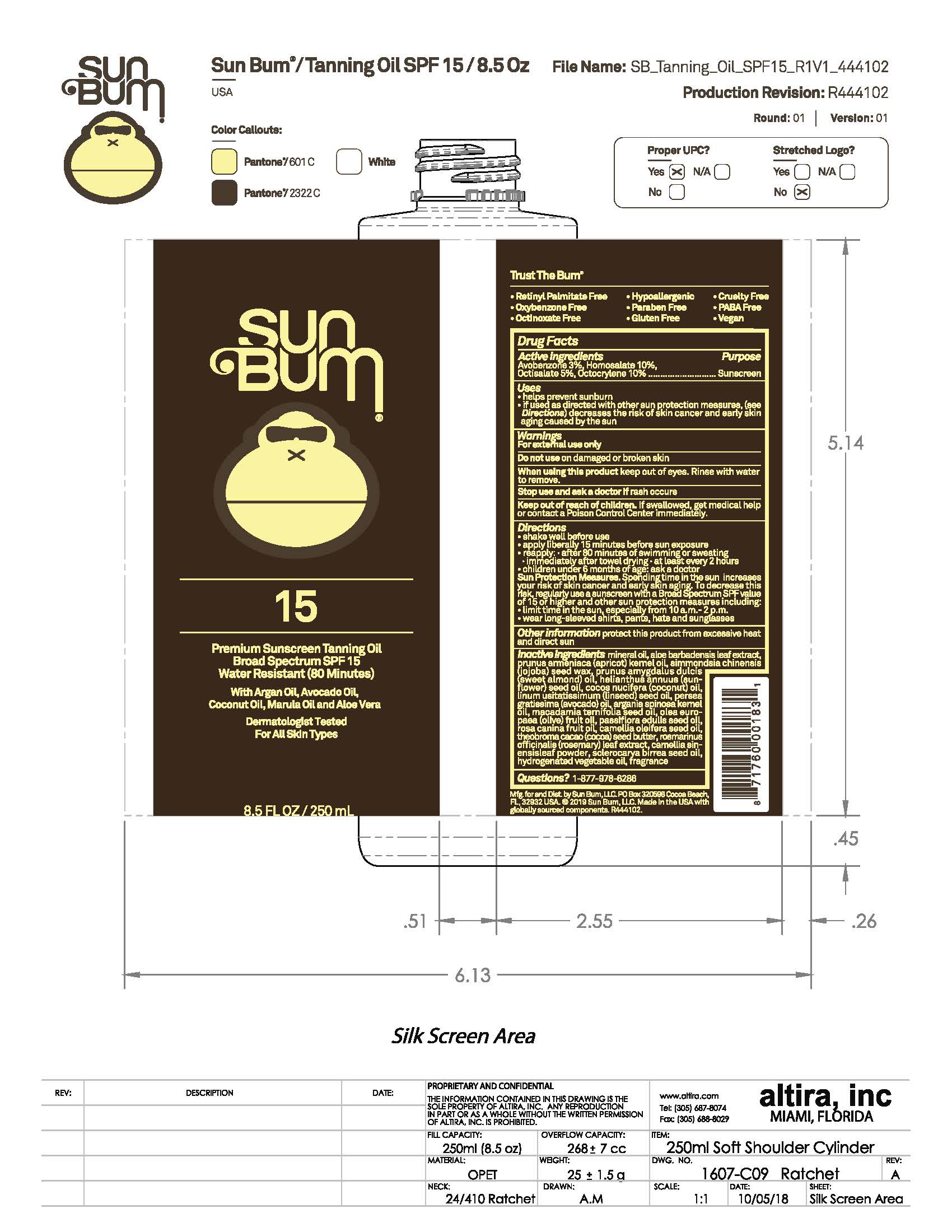 DRUG LABEL: Sun Bum 15 Premium Sunscreen Tanning Oil
NDC: 69039-794 | Form: OIL
Manufacturer: Sun Bum, LLC
Category: otc | Type: HUMAN OTC DRUG LABEL
Date: 20250826

ACTIVE INGREDIENTS: OCTOCRYLENE 100 mg/1 mL; OCTISALATE 50 mg/1 mL; AVOBENZONE 30 mg/1 mL; HOMOSALATE 100 mg/1 mL
INACTIVE INGREDIENTS: PRUNUS AMYGDALUS DULCIS (SWEET ALMOND) OIL; SCLEROCARYA BIRREA SEED OIL; ARGANIA SPINOSA KERNEL OIL; OLEA EUROPAEA (OLIVE) FRUIT OIL; ALOE BARBADENSIS LEAF; SIMMONDSIA CHINENSIS (JOJOBA) SEED WAX; LINUM USITATISSIMUM (LINSEED) SEED OIL; THEOBROMA CACAO (COCOA) SEED BUTTER; CAMELLIA SINENSIS LEAF; HELIANTHUS ANNUUS (SUNFLOWER) SEED OIL; COCOS NUCIFERA (COCONUT) OIL; PERSEA GRATISSIMA (AVOCADO) OIL; CORN OIL; APRICOT KERNEL OIL; PASSIFLORA EDULIS SEED OIL; MACADAMIA TERNIFOLIA SEED OIL; MINERAL OIL; CAMELLIA OLEIFERA SEED OIL; ROSA CANINA FRUIT OIL

Sun Bum 15 Premium Sunscreen Tanning Oil

Active Ingredients

Avobenzone 3%, Homosalate 10%, Octisalate 5%, Octocrylene 10%

Purpose

Sunscreen

Uses

• helps prevent sunburn • if used as directed with other sun protection measures, (see Directions) decreases the risk of skin cancer and early skin aging caused by the sun

Warnings

For external use only

Do not use on damaged or broken skin

When using this product keep out of eyes. Rinse with water to remove.

Stop use and ask a doctor if rash occurs

Keep out of reach of children. If swallowed, get medical help or contact a Poison Control Center immediately.

Warnings

Keep Out Of Reach Of Children

Directions

• shake well before use

• apply liberally 15 minutes before sun exposure

• reapply: • after 80 minutes of swimming or sweating • immediately after towel drying • at least every 2 hours

• children under 6 months of age: ask a doctor

• Sun Protection Measures. Spending time in the sun increases your risk of skin cancer and early skin aging. To decrease this risk, regularly use a sunscreen with a Broad Spectrum SPF value of 15 or higher and other sun protection measures including:

• limit time in the sun, especially from 10 a.m.- 2 p.m.

• wear long-sleeved shirts, pants, hats and sunglasses

Directions

• shake well before use

• apply liberally 15 minutes before sun exposure

Other Information

protect this product from excessive heat and direct sun

Inactive Ingredients

Mineral Oil, Aloe Barbadensis Leaf Extract, Prunus Armeniaca (Apricot) Kernel Oil, Simmondsia Chinensis (Jojoba) Seed Oil, Prunus Amygdalus Dulcis (Sweet Almond) Oil, Helianthus Annuus (Sunflower) Seed Oil, Cocos Nucifera (Coconut) Oil, Linum Usitatissimum (Linseed) Seed Oil, Persea Gratissima (Avocado) Oil, Argania Spinosa Kernel Oil, Macadamia Ternifolia Seed Oil, Olea Europaea (Olive) Fruit Oil, Passiflora Edulis Seed Oil, Rosa Canina Fruit Oil, Camellia Oleifera Seed Oil, Theobroma Cacao (Cocoa) Seed Butter, Camellia Sinensis Leaf Powder, Sclerocarya Birrea Seed Oil, Hydrogenated Vegetable Oil, Fragrance

Questions?

1-877-978-6286